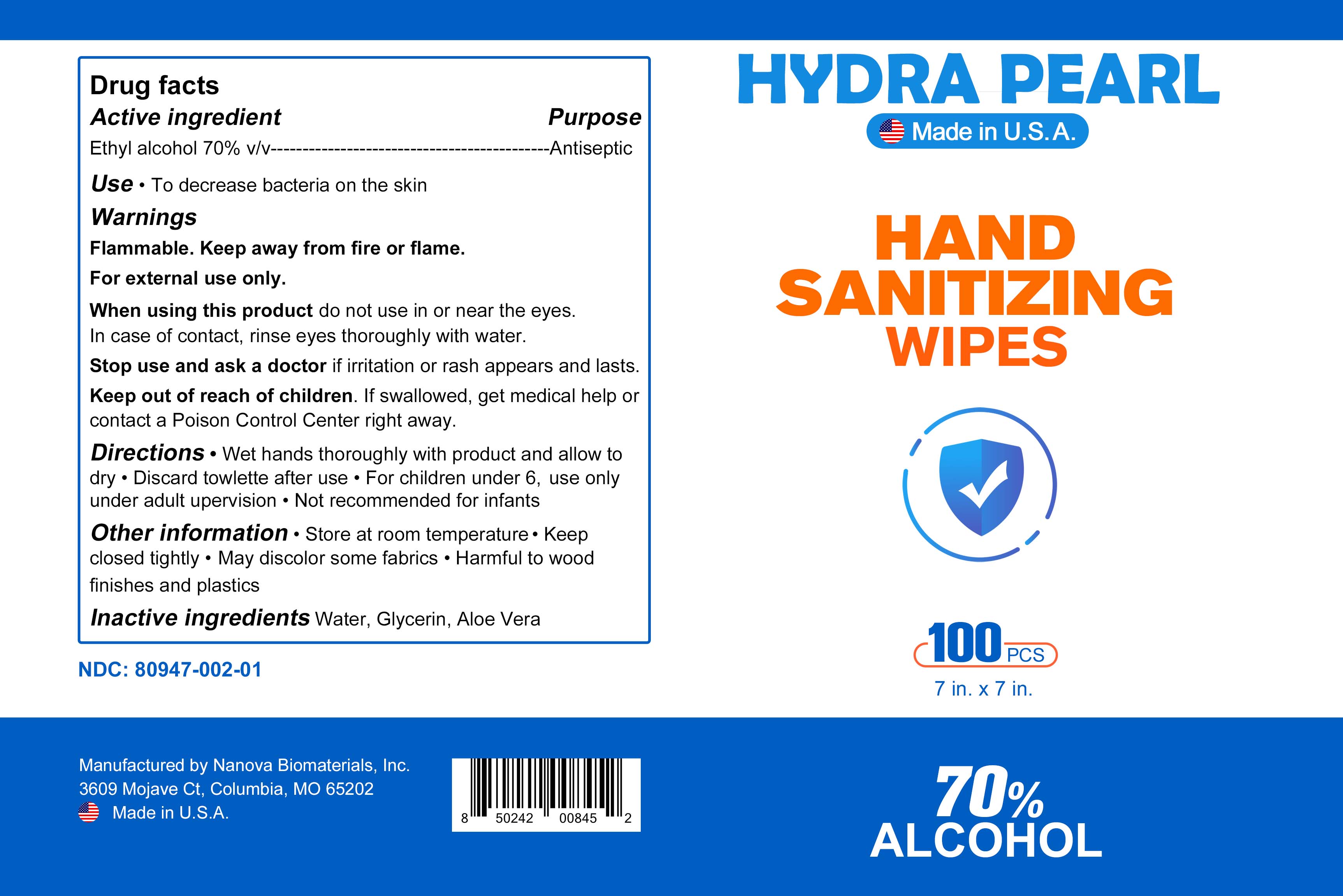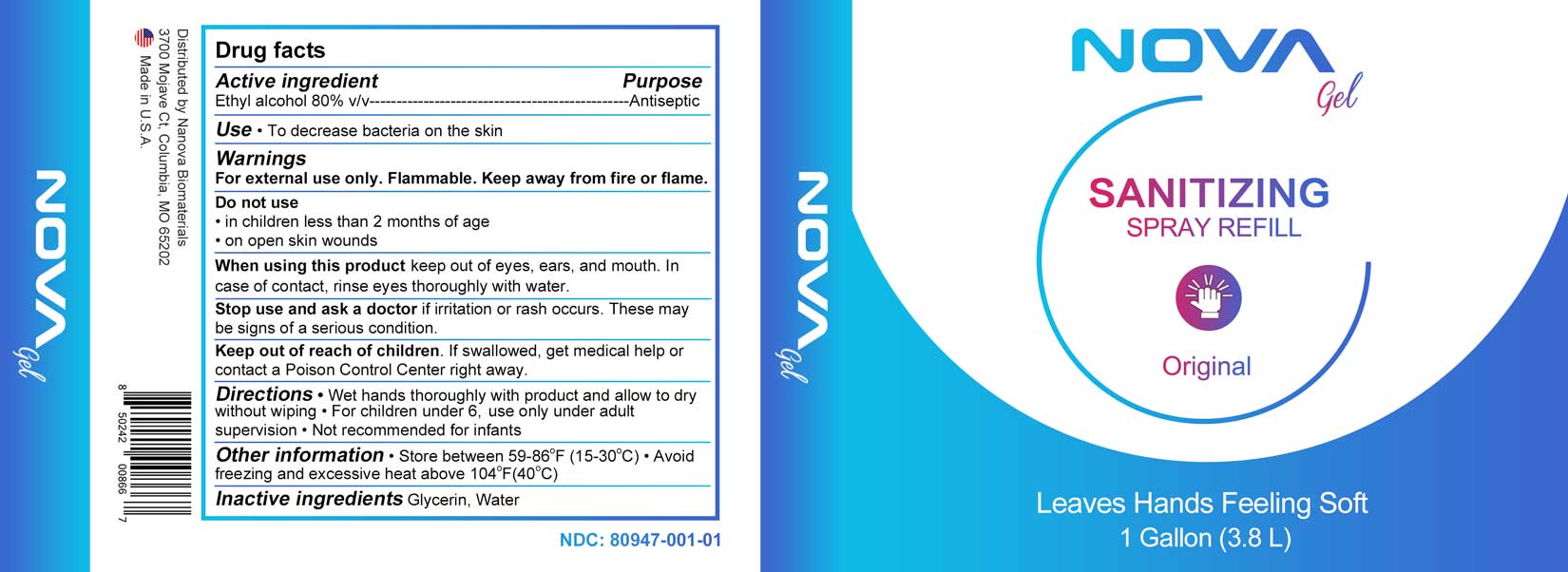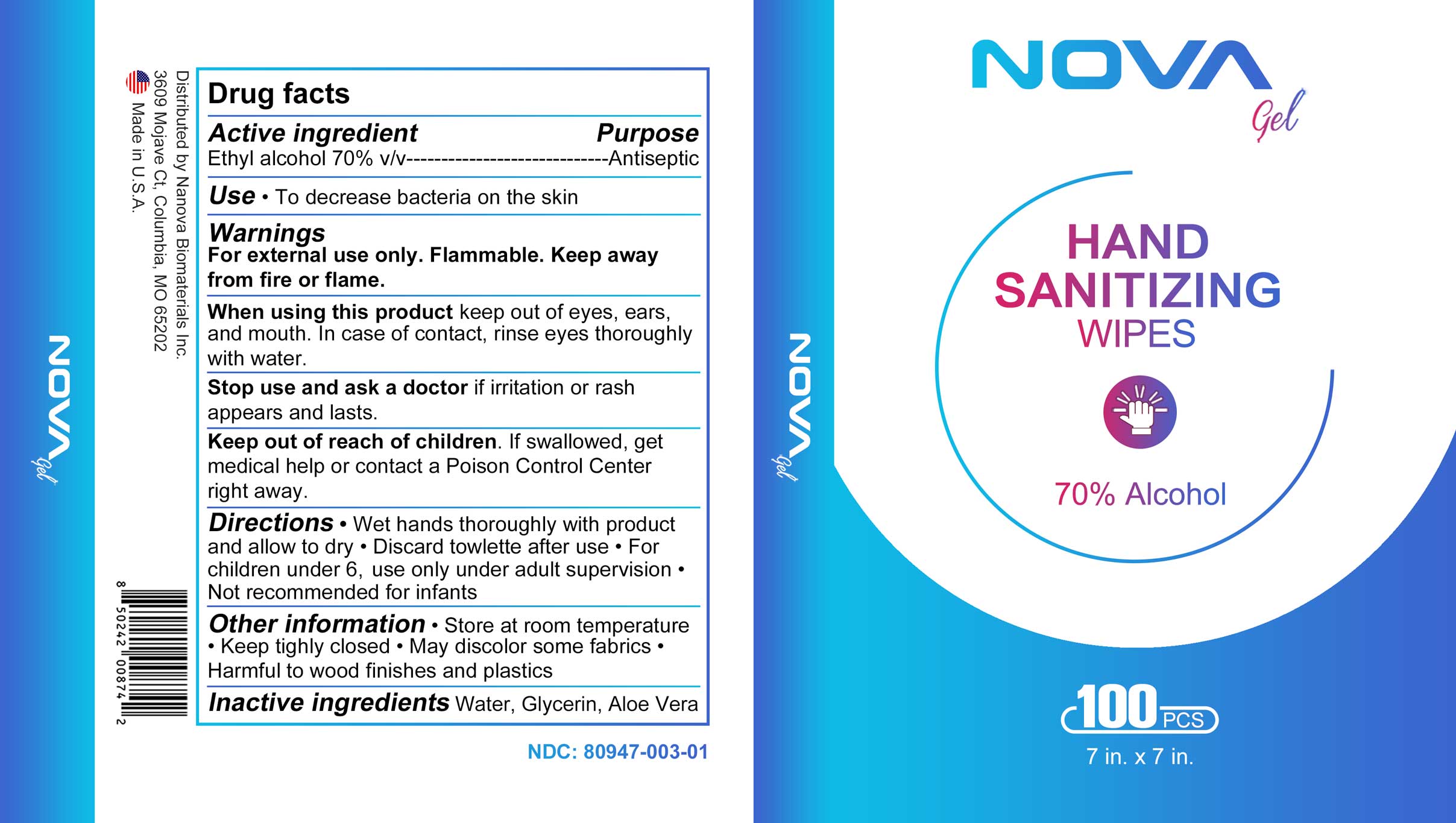 DRUG LABEL: NovaGel Wipes
NDC: 80947-003 | Form: LIQUID
Manufacturer: Nanova Biomaterials Inc
Category: otc | Type: HUMAN OTC DRUG LABEL
Date: 20210308

ACTIVE INGREDIENTS: ALCOHOL 490 mL/700 mL
INACTIVE INGREDIENTS: ALOE 0.35 mL/700 mL; WATER 200.2 mL/700 mL; GLYCERIN 9.45 mL/700 mL

Principle Display Panel

Active Ingredient

Ethyl Alcohol 80% v/v Antiseptic

Purpose Section

Use - To decrease bacteria on skin

Keep out of the reach of children

Keep out of reach of children

Use - To decrease bacteria on skin

Warnings

For external use only. Flammable. Keep away from fire and flame.

Dosage

Active Ingredient

Ethyl Alcohol 80% v/v

Inactive Ingredient Section

Inactive Ingredients

Glycerin, Water